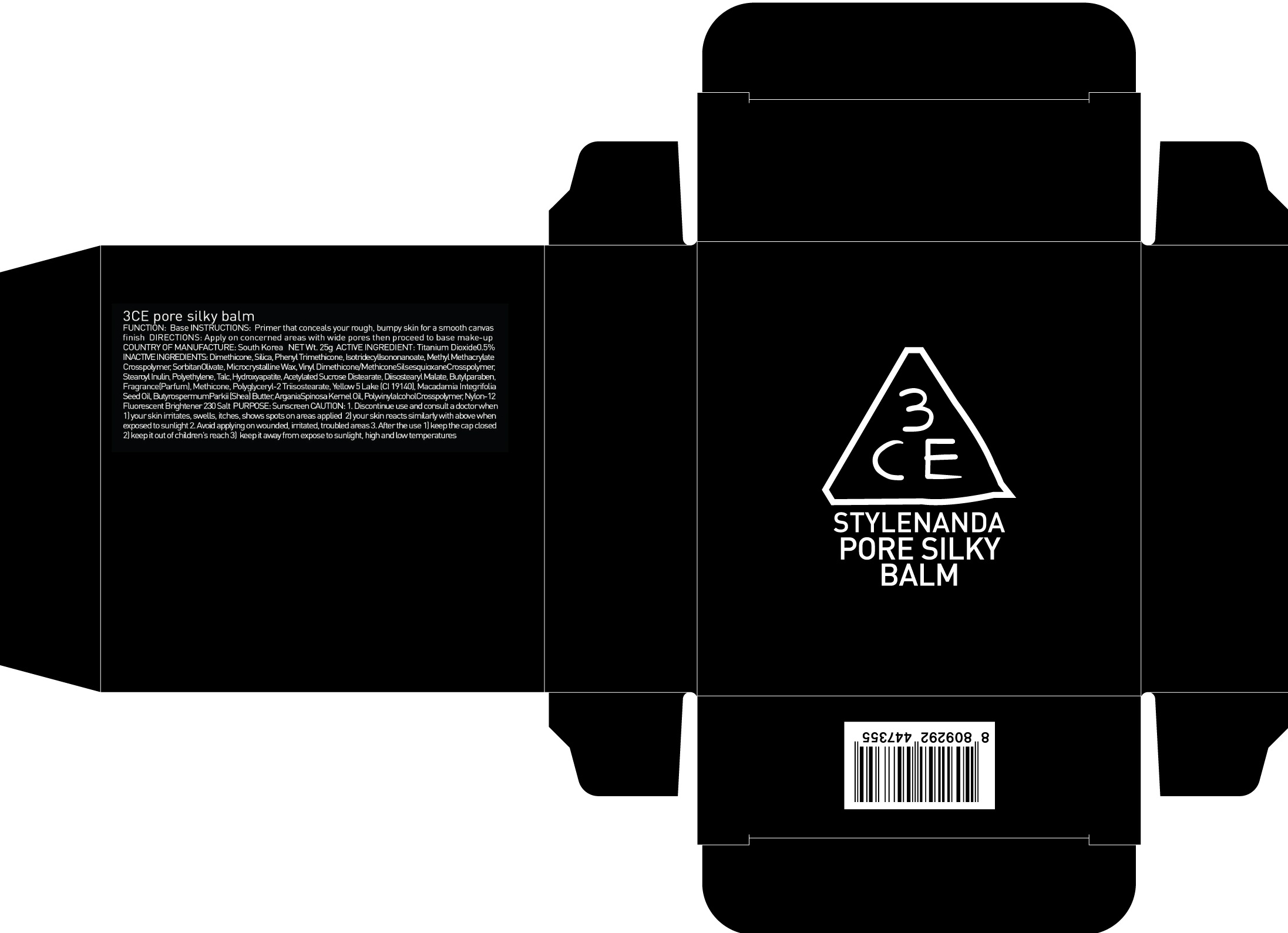 DRUG LABEL: 3CE PORE SILKY BALM
NDC: 60764-014 | Form: POWDER
Manufacturer: Nanda Co., Ltd
Category: otc | Type: HUMAN OTC DRUG LABEL
Date: 20160921

ACTIVE INGREDIENTS: Titanium Dioxide 0.12 g/25 g
INACTIVE INGREDIENTS: Dimethicone; Phenyl Trimethicone

ACTIVE INGREDIENT

Active Ingredient: Titanium Dioxide 0.5%

INACTIVE INGREDIENT

Inactive Ingredients: Dimethicone, Silica, Phenyl Trimethicone, IsotridecylIsononanoate, Methyl Methacrylate Crosspolymer, SorbitanOlivate, Microcrystalline Wax, Vinyl Dimethicone/MethiconeSilsesquioxaneCrosspolymer, Stearoyl Inulin, Polyethylene, Talc, Hydroxyapatite, Acetylated Sucrose Distearate, Diisostearyl Malate, Butylparaben, Fragrance(Parfum), Methicone, Polyglyceryl-2 Triisostearate, Yellow 5 Lake (CI 19140), Macadamia Integrifolia Seed Oil, ButyrospermumParkii (Shea) Butter, ArganiaSpinosa Kernel Oil, PolyvinylalcoholCrosspolymer, Nylon-12 Fluorescent Brightener 230 Salt

PURPOSE

Purpose: Sunscreen

CAUTION

CAUTION: 1. Discontinue use and consult a doctor when - your skin irritates, swells, itches, shows spots on areas applied - your skin reacts similarly with above when exposed to sunlight 2. Avoid applying on wounded, irritated, troubled areas 3. After the use - keep the cap closed - keep it out of children's reach - keep it away from expose to sunlight, high and low temperatures

DESCRIPTION

INSTRUCTIONS: Primer that conceals your rough, bumpy skin for a smooth canvas finish.

Directions: Apply on concerned areas with wide pores then proceed to base make-up.